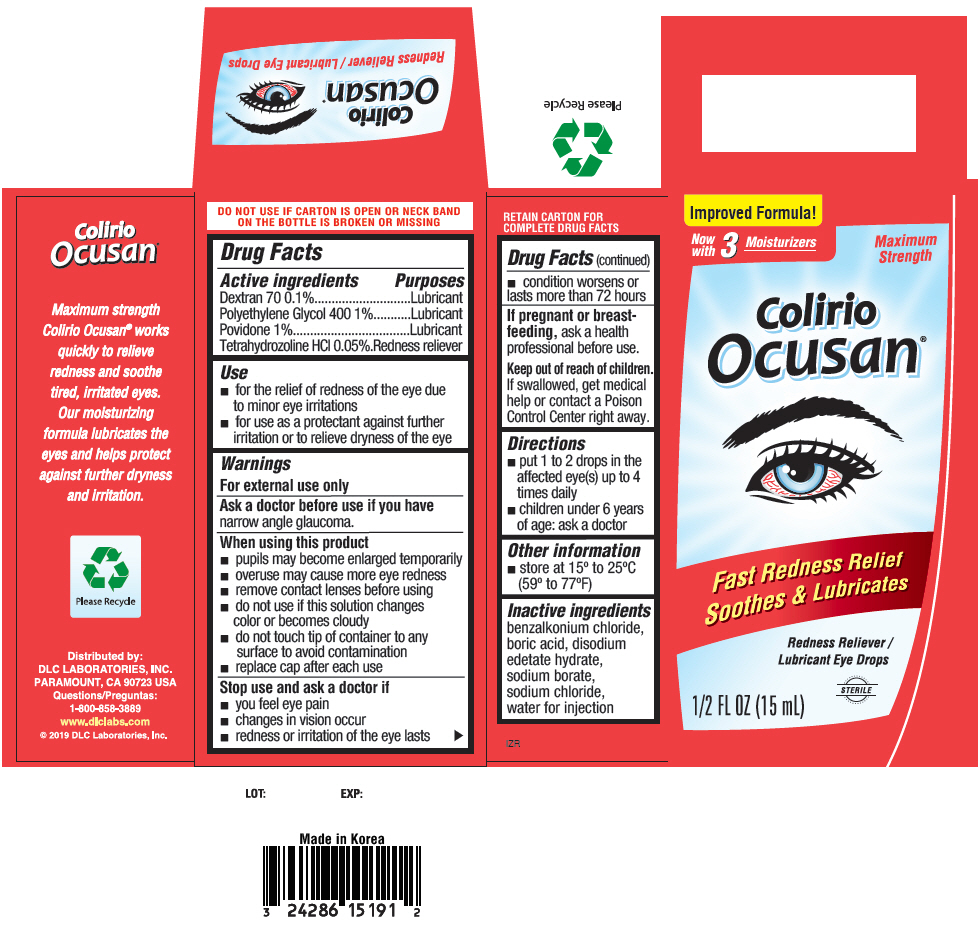 DRUG LABEL: Colirio Ocusan
NDC: 24286-1575 | Form: LIQUID
Manufacturer: DLC Laboratories, Inc.
Category: otc | Type: HUMAN OTC DRUG LABEL
Date: 20250418

ACTIVE INGREDIENTS: TETRAHYDROZOLINE HYDROCHLORIDE 0.5 mg/1 mL; POLYETHYLENE GLYCOL 400 10 mg/1 mL; POVIDONE, UNSPECIFIED 10 mg/1 mL; DEXTRAN 70 1 mg/1 mL
INACTIVE INGREDIENTS: BORIC ACID; SODIUM BORATE; EDETATE DISODIUM; BENZALKONIUM CHLORIDE; SODIUM CHLORIDE; WATER

Colirio Ocusan®

Drug Facts

ACTIVE INGREDIENT

PURPOSE

Active ingredients | Purposes
Dextran 70 0.1% | Lubricant
Polyethylene Glycol 400 1% | Lubricant
Povidone 1% | Lubricant
Tetrahydrozoline HCl 0.05% | Redness reliever

Use

- for the relief of redness of the eye due to minor eye irritations
- for use as a protectant against further irritation or to relieve dryness of the eye

Warnings

For external use only

Ask a doctor before use if you havenarrow angle glaucoma.

When using this product

- pupils may become enlarged temporarily
- overuse may cause more eye redness
- remove contact lenses before using
- do not use if this solution changes color or becomes cloudy
- do not touch tip of container to any surface to avoid contamination
- replace cap after each use

Stop use and ask a doctor if

- you feel eye pain
- changes in vision occur
- redness or irritation of the eye lasts
- condition worsens or lasts more than 72 hours

PREGNANCY OR BREAST FEEDING

If pregnant or breastfeeding,ask a health professional before use.

Keep out of reach of children.If swallowed, get medical help or contact a Poison Control Center right away.

Directions

- put 1 to 2 drops in the affected eye(s) up to 4 times daily
- children under 6 years of age: ask a doctor

Other information

- store at 15° to 25°C (59° to 77°F)

Inactive ingredients

benzalkonium chloride, boric acid, disodium edetate hydrate, sodium borate, sodium chloride, water for injection

Questions

1-800-858-3889

Distributed by:
DLC LABORATORIES, INC.
PARAMOUNT, CA 90723 USA

PRINCIPAL DISPLAY PANEL - 15 mL Bottle Box

Improved Formula!

Now
with
3
Moisturizers

Maximum
Strength

Colirio
Ocusan®

Fast Redness Relief
Soothes & Lubricates

Redness Reliever /
Lubricant Eye Drops

STERILE

1/2 FL OZ (15 mL)